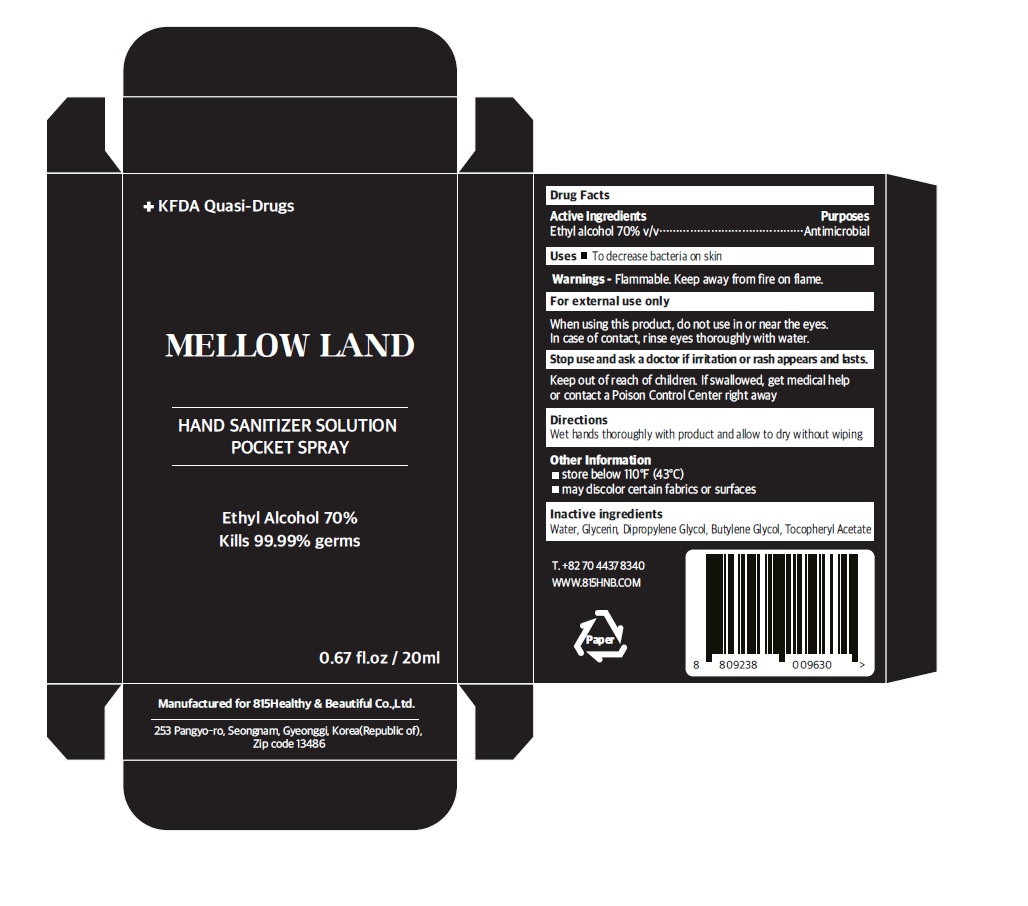 DRUG LABEL: Mellow Land Hand Sanitizer Solution
NDC: 79210-001 | Form: SPRAY
Manufacturer: 815Healthy & Beautiful Co.,Ltd.
Category: otc | Type: HUMAN OTC DRUG LABEL
Date: 20200623

ACTIVE INGREDIENTS: ALCOHOL 0.7 mL/1 mL
INACTIVE INGREDIENTS: WATER; GLYCERIN; DIPROPYLENE GLYCOL; BUTYLENE GLYCOL; .ALPHA.-TOCOPHEROL ACETATE

79210-100_Mellow Land Hand Sanitizer Solution

Active ingredient

Ethyl alcohol 70% v/v

Purpose

Antimicrobial

Use

- To decrease bacteria on skin

Warnings

Flammable. Keep away from fire or flame.

For external use only

When using this product do not use in or near the eyes. In case of contact, rinse eyes thoroughly with water.

Stop use and ask a doctor if irritation or rash appears and lasts

Keep out of reach of children.

Other information

- Store below 110°F (43°C)
- May discolor certain fabrics or surfaces

Directions

Wet hands thoroughly with product and allow to dry without wiping

Inactive ingredients

Water, Glycerin, Dipropylene Glycol, Butylene Glycol, Tocopheryl Acetate